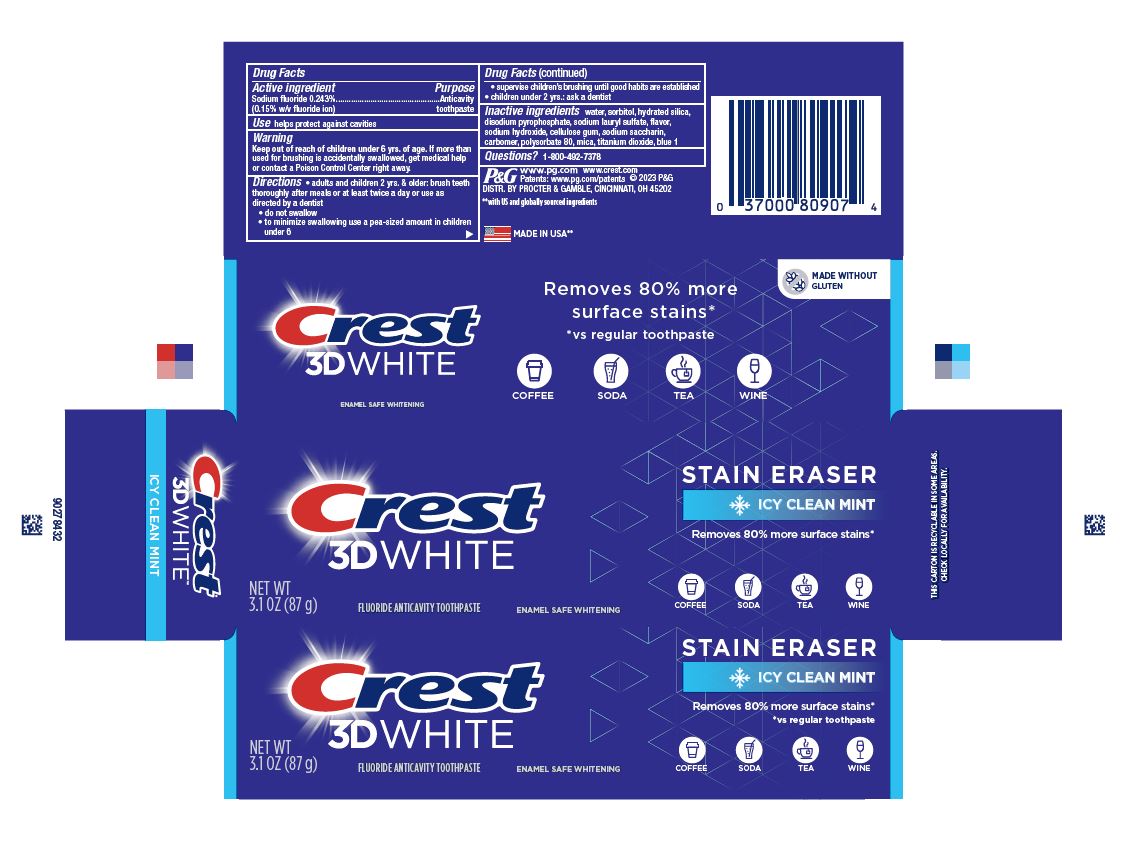 DRUG LABEL: Crest 3D White
NDC: 69423-773 | Form: PASTE, DENTIFRICE
Manufacturer: The Procter & Gamble Manufacturing Company
Category: otc | Type: HUMAN OTC DRUG LABEL
Date: 20260203

ACTIVE INGREDIENTS: SODIUM FLUORIDE 1.5 mg/1 g
INACTIVE INGREDIENTS: CARBOXYPOLYMETHYLENE; POLYSORBATE 80; HYDRATED SILICA; TITANIUM DIOXIDE; CARBOXYMETHYLCELLULOSE SODIUM; SORBITOL; SACCHARIN SODIUM; SODIUM LAURYL SULFATE; SODIUM HYDROXIDE; SODIUM ACID PYROPHOSPHATE; WATER; FD&C BLUE NO. 1; MICA

Crest 3D White Stain Eraser Icy Clean Mint

Drug Facts

Sodium fluoride 0.243%

(0.15% w/v fluoride ion)

Purpose

Anticavity toothpaste

Use

helps protect against cavities

Warning

Keep out of reach of children under 6 yrs. of age. If more than used for brushing is accidentally swallowed, get medical help or contact a Poison Control Center right away.

Directions

- adults and children 2 yrs. & older: brush teeth thoroughly after meals or at least twice a day or use as directed by a dentist
- do not swallow
- to minimize swallowing use a pea-sized amount in children under 6
- supervise children's brushing until good habits are established
- children under 2 yrs.: ask a dentist

Inactive ingredients

water, sorbitol, hydrated silica, disodium pyrophosphate, sodium lauryl sulfate, flavor, sodium hydroxide, cellulose gum, sodium saccharin, carbomer, polysorbate 80, mica, titanium dioxide, blue 1

Questions?

1-800-492-7378

DISTR. BY PROCTER & GAMBLE, CINCINNATI, OH 45202

Crest 3D White Stain Eraser Icy Clean Mint

Crest

3D White

Fluoride Anticavity Toothpaste

Enamel Safe Whitening

NET WT 3.1 OZ (87 g)

Stain Eraser

Icy Clean Mint

Removes up to 80% of surface stains*

Coffee Soda Tea Wine